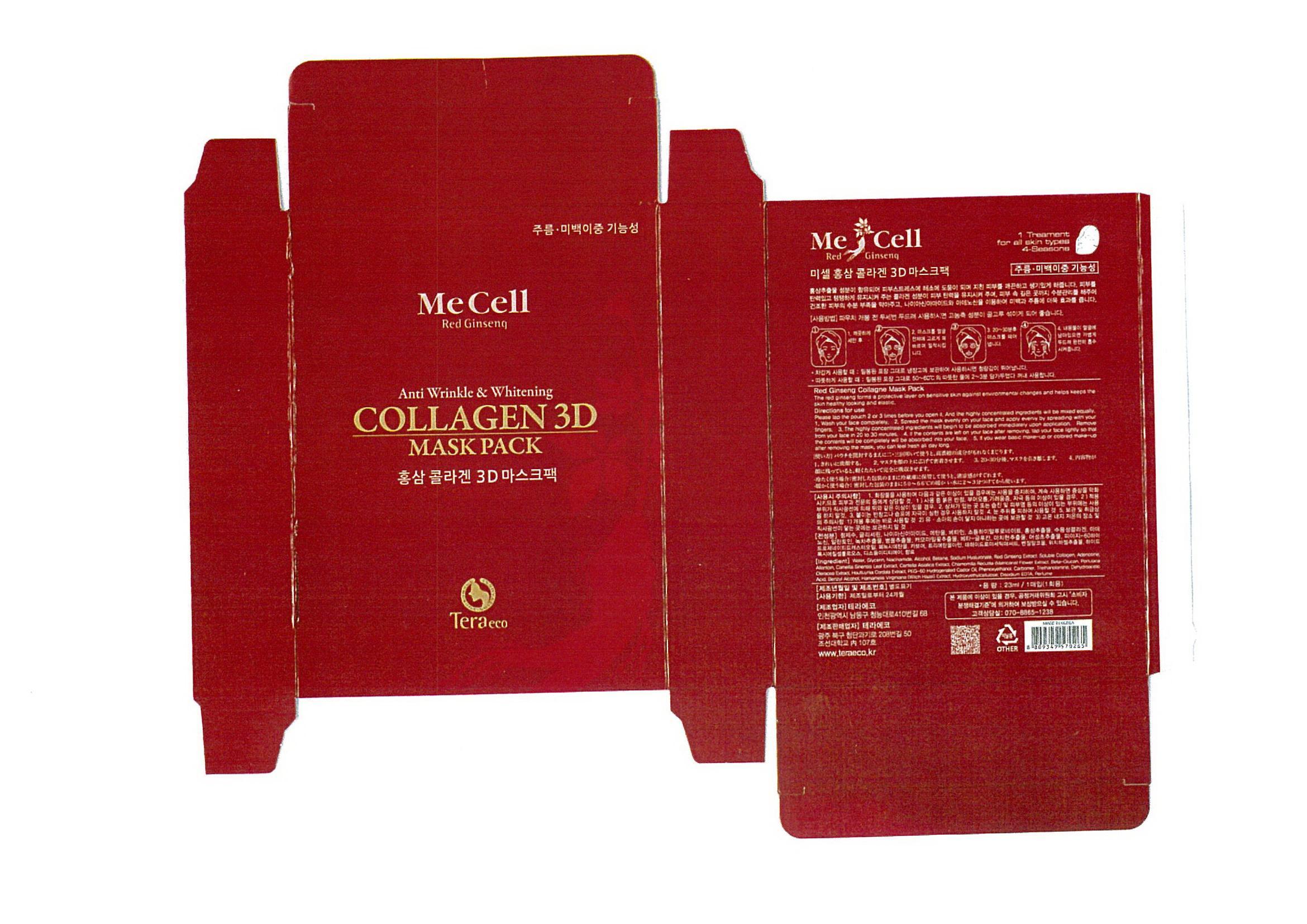 DRUG LABEL: Mecell Red Ginseng Collagen 3D Mask Pack
NDC: 69463-2001 | Form: LIQUID
Manufacturer: TERAECO 
Category: otc | Type: HUMAN OTC DRUG LABEL
Date: 20141228

ACTIVE INGREDIENTS: GLYCERIN 0.03 g/1 g
INACTIVE INGREDIENTS: WATER; NIACINAMIDE; ADENOSINE

Drug Facts

ACTIVE INGREDIENT

glycerin

INACTIVE INGREDIENT

water, niacinamide, adenosine, ethanol, betaine, sodium hyaluronate, etc

PURPOSE

anti wrinkle
whitening

keep out of reach of the children

INDICATIONS AND USAGE

apply to the skin and leave on for 20 to 30 minutes

WARNINGS

keep in a cool placedo not store in high temperature condition

DOSAGE AND ADMINISTRATION

for external use only